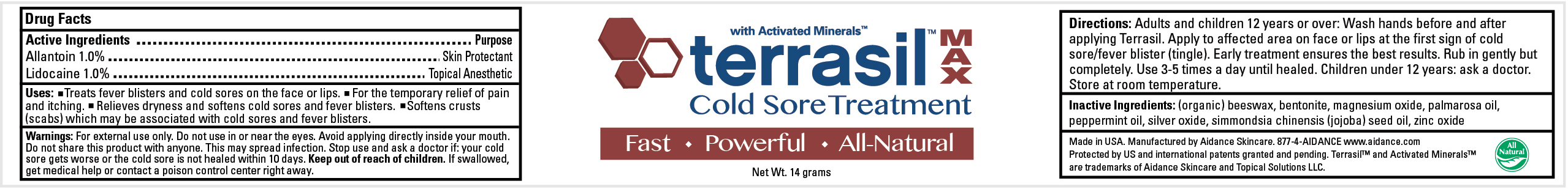 DRUG LABEL: TERRASIL COLD SORE TREATMENT
								
NDC: 24909-110 | Form: OINTMENT
Manufacturer: Aidance Skincare & Topical Solutions, LLC
Category: otc | Type: HUMAN OTC DRUG LABEL
Date: 20120201

ACTIVE INGREDIENTS: Allantoin 1 g/100 g; Lidocaine 1 g/100 g
INACTIVE INGREDIENTS: BENTONITE; JOJOBA OIL; MAGNESIUM OXIDE; PALMAROSA OIL; PEPPERMINT OIL; SILVER OXIDE; WHITE WAX; ZINC OXIDE

Drug Facts

Active Ingredient

Allantoin 1.0%, Lidocaine 1.0%

Purpose

Allantoin - Skin Protectant
Lidocaine - Topical Anesthetic

Uses

Treats fever blisters and cold sores on the face or lips.
For the temporary relief of pain and itching.
Relieves dryness and softens cold sores and fever blisters.
Softens crusts (scabs) which may be associated with cold sores and fever blisters.

Warnings

For external use only. Do not use in or near the eyes. Avoid applying directly inside your mouth. Do not share this product with anyone. This may spread infection. Stop use and ask a doctor if: your cold sore gets worse or the cold sore is not healed within 10 days.

Keep out of reach of children.

If swallowed, get medical help or contact a poison control center right away.

Directions

Adults and children 12 years or over: Wash hands before and after applying Terrasil. Apply to affected area on face or lips at the first sign of cold sore/fever blister (tingle). Early treatment ensures the best results. Rub in gently but completely. Use 3-5 times a day until healed. Children under 12 years: ask a doctor. Store at room temperature.

Inactive Ingredients

(organic) beeswax, bentonite, magnesium oxide, palmarosa oil, peppermint oil, silver oxide, simmondsia chinensis (jojoba) seed oil, zinc oxide

PACKAGE LABEL

.